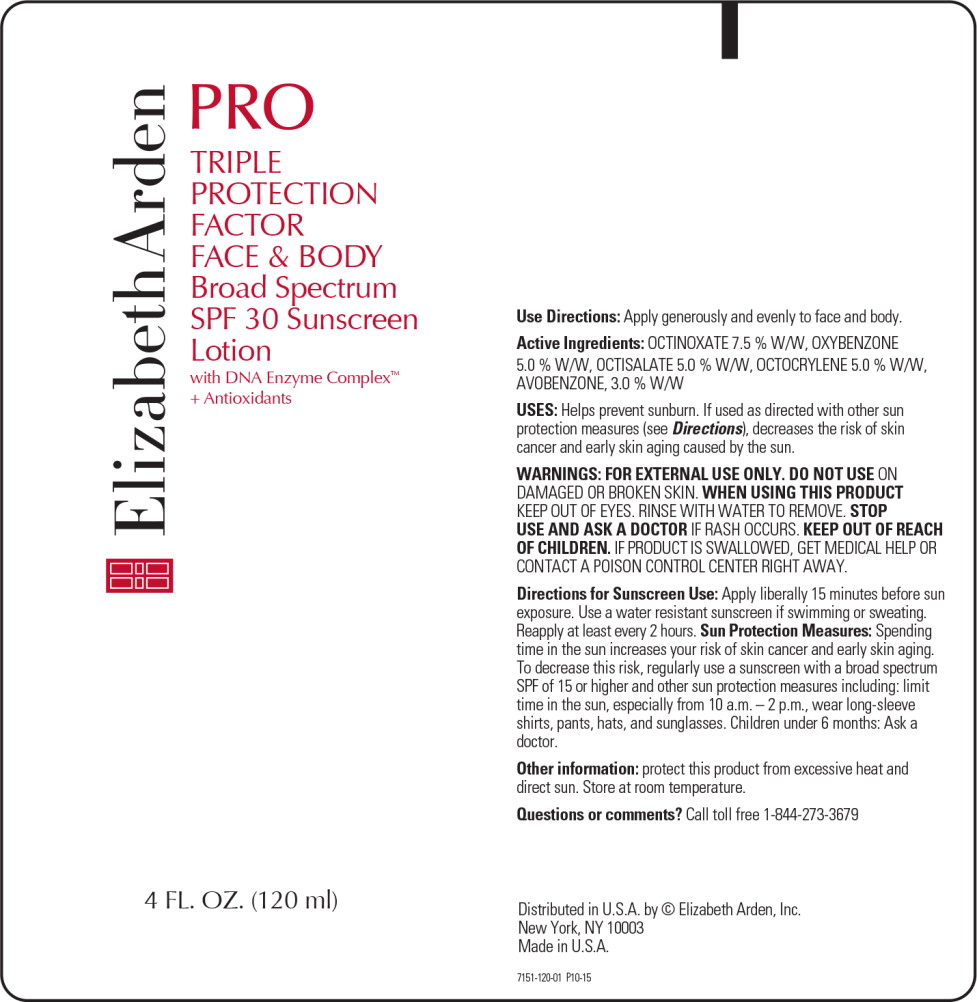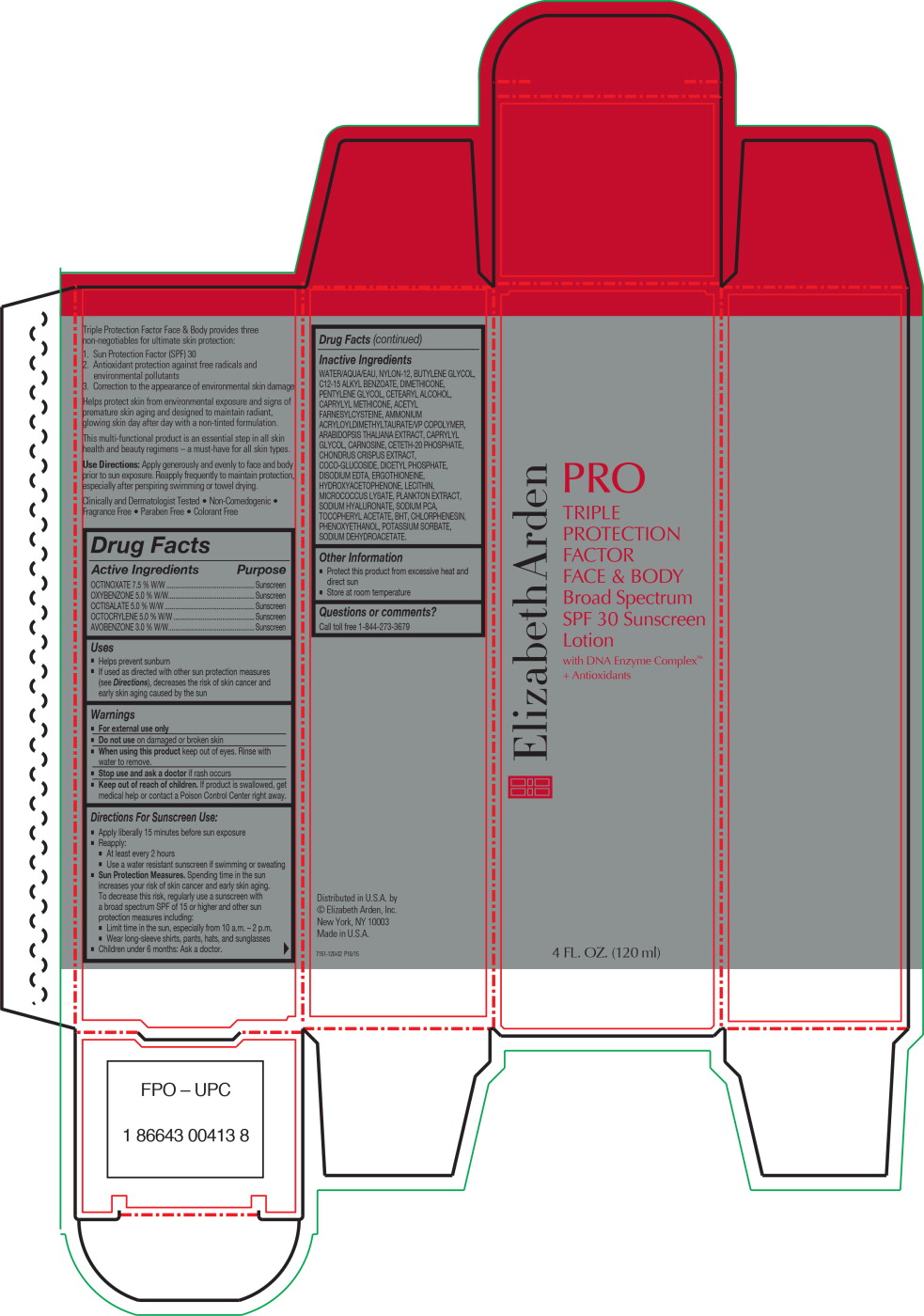 DRUG LABEL: PRO TRIPLE PROTECTION FACTOR FACE AND BODY BROAD SPECTRUM SPF 30 SUNSCREEN
NDC: 67938-2076 | Form: LOTION
Manufacturer: ELIZABETH ARDEN, INC
Category: otc | Type: HUMAN OTC DRUG LABEL
Date: 20170201

ACTIVE INGREDIENTS: OCTINOXATE .07575 g/1 mL; OXYBENZONE .06 g/1 mL; OCTISALATE .0505 g/1 mL; OCTOCRYLENE .0525 g/1 mL; AVOBENZONE .03237 g/1 mL
INACTIVE INGREDIENTS: WATER; NYLON-12; BUTYLENE GLYCOL; ALKYL (C12-15) BENZOATE; PENTYLENE GLYCOL; DIMETHICONE; CETOSTEARYL ALCOHOL; CAPRYLYL TRISILOXANE; CETETH-20 PHOSPHATE; PHENOXYETHANOL; AMMONIUM ACRYLOYLDIMETHYLTAURATE/VP COPOLYMER; COCO GLUCOSIDE; CARNOSINE; DIHEXADECYL PHOSPHATE; SODIUM PYRROLIDONE CARBOXYLATE; CAPRYLYL GLYCOL; .ALPHA.-TOCOPHEROL ACETATE; CHLORPHENESIN; ACETYL FARNESYLCYSTEINE; EDETATE DISODIUM ANHYDROUS; CHONDRUS CRISPUS CARRAGEENAN; BUTYLATED HYDROXYTOLUENE; LECITHIN, SOYBEAN; POTASSIUM SORBATE; ARABIDOPSIS THALIANA; SODIUM DEHYDROACETATE; ERGOTHIONEINE; HYALURONATE SODIUM

Drug Facts

Active Ingredients

OCTINOXATE 7.5 % W/W

OXYBENZONE 5.0 % W/W

OCTISALATE 5.0 % W/W

OCTOCRYLENE 5.0 % W/W

AVOBENZONE 3.0 % W/W

Purpose

Sunscreen

Sunscreen

Sunscreen

Sunscreen

Sunscreen

Uses

- Helps prevent sunburn
- If used as directed with other sun protection measures (see Directions), decreases the risk of skin cancer and early skin aging caused by the sun

Warnings

- For external use only

- Do not use on damaged or broken skin

- When using this product keep out of eyes. Rinse with water to remove.

- Stop use and ask a doctor if rash occurs

- Keep out of reach of children. If product is swallowed, get medical help or contact a Poison Control Center right away.

Directions For Sunscreen Use:

- Apply liberally 15 minutes before sun exposure
- Reapply:
  - At least every 2 hours
  - Use a water resistant sunscreen if swimming or sweating
- Sun Protection Measures. Spending time in the sun increases your risk of skin cancer and early skin aging. To decrease this risk, regularly use a sunscreen with a broad spectrum SPF of 15 or higher and other sun protection measures including:
  - Limit time in the sun, especially from 10 a.m. – 2 p.m.
  - Wear long-sleeve shirts, pants, hats, and sunglasses
- Children under 6 months: Ask a doctor.

Inactive Ingredients

WATER/AQUA/EAU, NYLON-12, BUTYLENE GLYCOL, C12-15 ALKYL BENZOATE, DIMETHICONE, PENTYLENE GLYCOL, CETEARYL ALCOHOL, CAPRYLYL METHICONE, ACETYL FARNESYLCYSTEINE, AMMONIUM ACRYLOYLDIMETHYLTAURATE/VP COPOLYMER, ARABIDOPSIS THALIANA EXTRACT, CAPRYLYL GLYCOL, CARNOSINE, CETETH-20 PHOSPHATE, CHONDRUS CRISPUS EXTRACT, COCO-GLUCOSIDE, DICETYL PHOSPHATE, DISODIUM EDTA, ERGOTHIONEINE, HYDROXYACETOPHENONE, LECITHIN, MICROCOCCUS LYSATE, PLANKTON EXTRACT, SODIUM HYALURONATE, SODIUM PCA, TOCOPHERYL ACETATE, BHT, CHLORPHENESIN, PHENOXYETHANOL, POTASSIUM SORBATE, SODIUM DEHYDROACETATE.

Other Information

- Protect this product from excessive heat and direct sun
- Store at room temperature

Questions or comments?

Call toll free 1-844-273-3679

Principal Display Panel - Bottle Label

ElizabethArden

PRO

TRIPLE
PROTECTION
FACTOR
FACE & BODY

Broad Spectrum
SPF 30 Sunscreen
Lotion

with DNA Enzyme Complex™
+ Antioxidants

4 FL. OZ. (120 ml)

Principal Display Panel - Carton Label

ElizabethArden

PRO

TRIPLE
PROTECTION
FACTOR
FACE & BODY

Broad Spectrum
SPF 30 Sunscreen
Lotion

with DNA Enzyme Complex™
+ Antioxidants

4 FL. OZ. (120 ml)